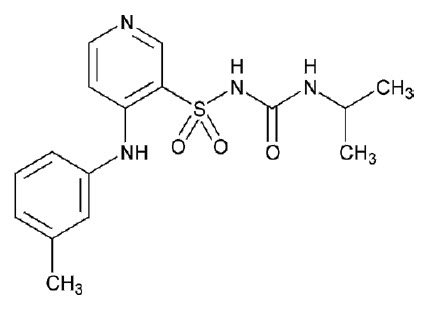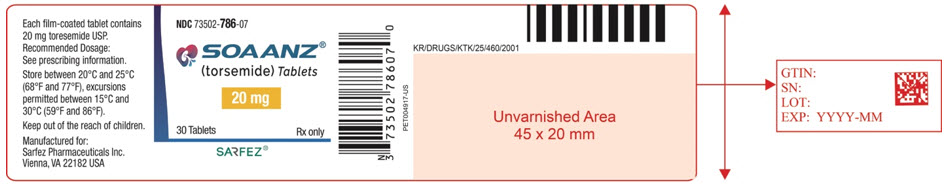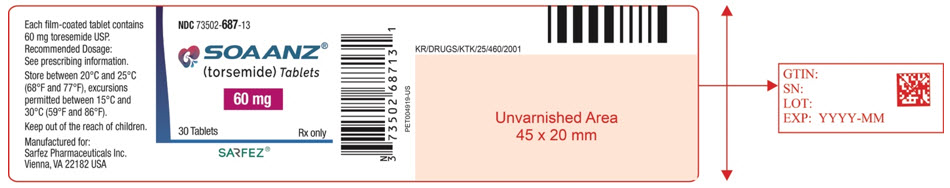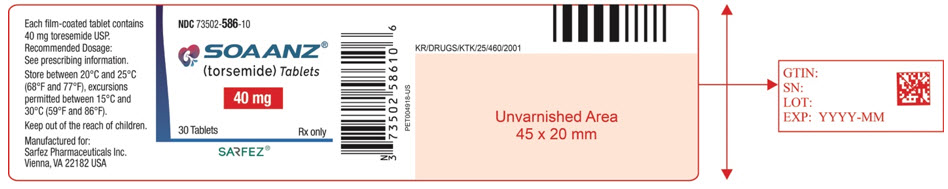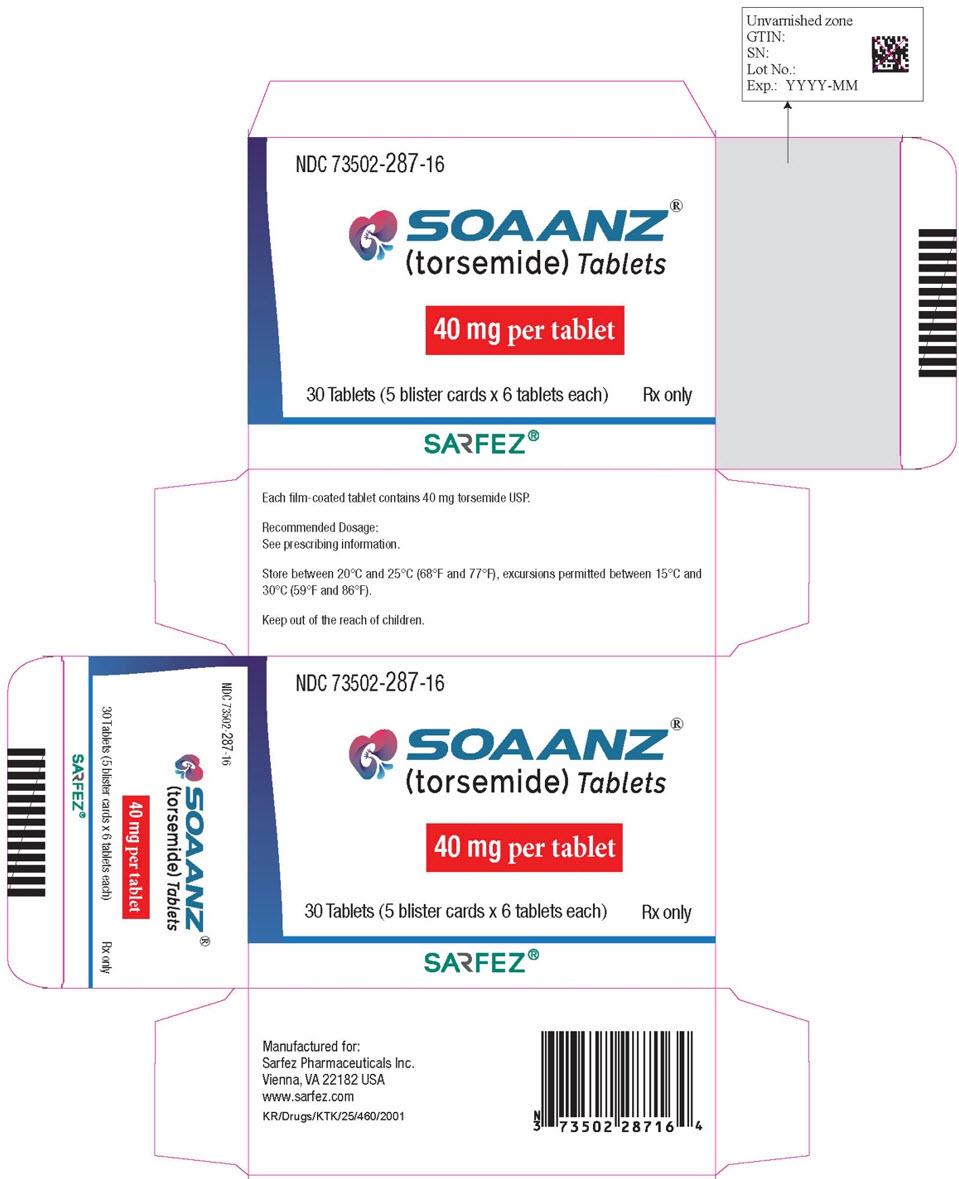 DRUG LABEL: SOAANZ
NDC: 73502-786 | Form: TABLET, FILM COATED
Manufacturer: Sarfez Pharmaceuticals Inc
Category: prescription | Type: HUMAN PRESCRIPTION DRUG LABEL
Date: 20260109

ACTIVE INGREDIENTS: TORSEMIDE 20 mg/1 1

Drug Structure

Structure Drug

Sample Image 40 mg

Sample Image of container Label for 40 mg.

soanzxr-06.jpg

Sample image 20 mg

soanzxr-02.jpg

Sample Image 60 mg

soanzxr-04.jpg

Sample Carton Image 40 mg

40 mg carton image

soanzxr-10.jpg